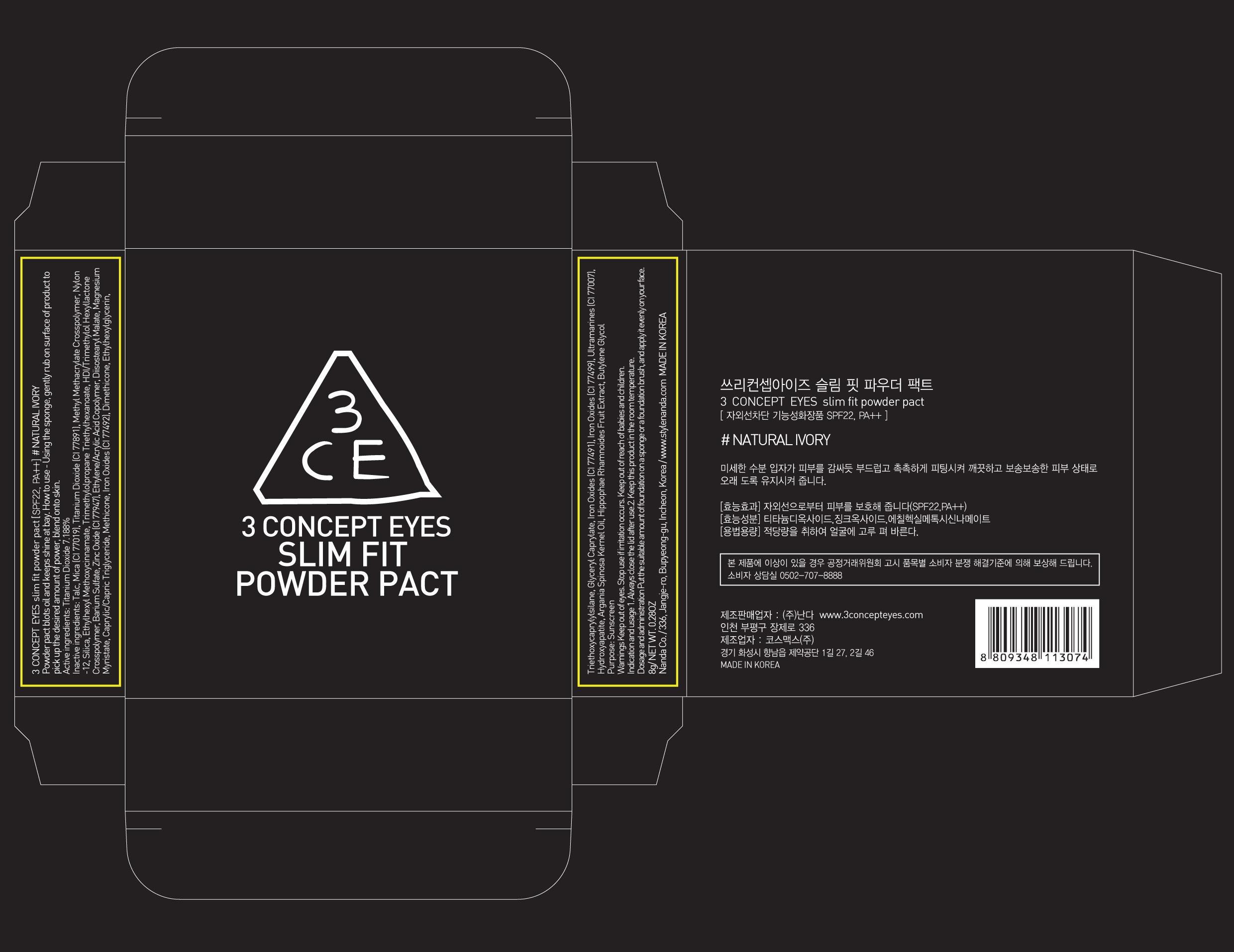 DRUG LABEL: 3 CONCEPT EYES SLIM FIT PACT NATURAL IVORY
NDC: 60764-009 | Form: POWDER
Manufacturer: NANDA CO., LTD.
Category: otc | Type: HUMAN OTC DRUG LABEL
Date: 20131003

ACTIVE INGREDIENTS: Titanium Dioxide 0.57 g/8 g
INACTIVE INGREDIENTS: Talc; Mica

ACTIVE INGREDIENT

Active ingredients: Titanium Dioxide 7.188%

INACTIVE INGREDIENT

Inactive ingredients: Talc, Mica (CI 77019), Methyl Methacrylate Crosspolymer, Nylon-12, Silica, Ethylhexyl Methoxycinnamate, Trimethylolpropane Triethylhexanoate, HDI/Trimethylol Hexyllactone Crosspolymer, Barium Sulfate, Zinc Oxide (CI 77947), Ethylene/Acrylic Acid Copolymer, Diisostearyl Malate, Magnesium Myristate, Caprylic/Capric Triglyceride, Methicone, Iron Oxides (CI 77492), Dimethicone, Ethylhexylglycerin, Triethoxycaprylylsilane, Glyceryl Caprylate, Iron Oxides (CI 77491), Iron Oxides (CI 77499), Ultramarines (CI 77007), Hydroxyapatite, Argania Spinosa Kernel Oil, Hippophae Rhamnoides Fruit Extract, Butylene Glycol

PURPOSE

Purpose: Sunscreen

WARNINGS

Warnings Keep out of eyes. Stop use if irritation occurs. Keep out of reach of babies and children.

KEEP OUT OF REACH OF CHILDREN

Keep out of reach of babies and children.

INDICATIONS AND USAGE

Indication and usage 1. Always close the lid after use.2. Keep this product in the room temperature.

Dosage and administration Apply suitable amount of powder evenly with a sponge on your face.